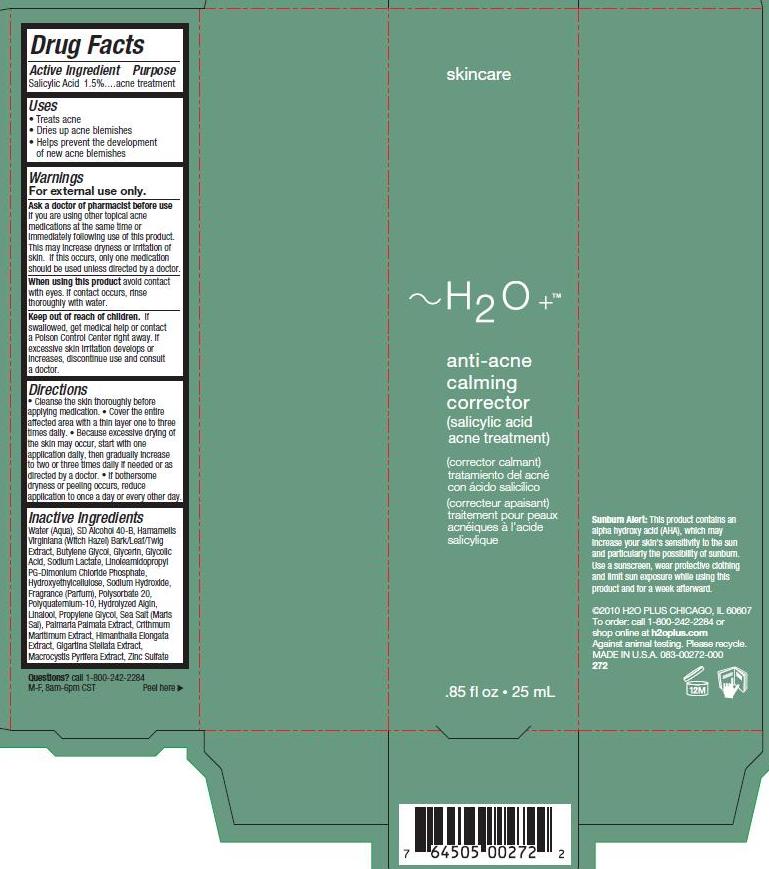 DRUG LABEL: Anti Acne Calming Corrector
NDC: 65903-272 | Form: GEL
Manufacturer: H2O Plus
Category: otc | Type: HUMAN OTC DRUG LABEL
Date: 20110928

ACTIVE INGREDIENTS: Salicylic Acid 15 uL/1 mL
INACTIVE INGREDIENTS: Water; ALCOHOL; HAMAMELIS VIRGINIANA BARK; BUTYLENE GLYCOL; GLYCERIN; GLYCOLIC ACID; SODIUM LACTATE; LINOLEAMIDOPROPYL PG-DIMONIUM CHLORIDE PHOSPHATE; HYDROXYETHYL CELLULOSE (2000 CPS AT 1%); SODIUM HYDROXIDE; POLYSORBATE 20; POLYQUATERNIUM-10 (400 CPS AT 2%); LINALOOL, (+/-)-; PROPYLENE GLYCOL; SEA SALT; DULSE; CRITHMUM MARITIMUM; HIMANTHALIA ELONGATA; MASTOCARPUS STELLATUS; MACROCYSTIS PYRIFERA; ZINC SULFATE

Drug Facts

Active Ingredient
Salicylic Acid 1.5%

Purpose
acne treatment

Warnings
For external use only.

Ask a doctor of pharmacist before use
if you are using other topical acne
medications at the same time or
immediately following use of this product.
This may increase dryness or irritation of
skin. If this occurs, only one medication
should be used unless directed by a doctor.

When using this product avoid contact
with eyes. If contact occurs, rinse
thoroughly with water.

Keep out of reach of children. If
swallowed, get medical help or contact
a Poison Control Center right away. If
excessive skin irritation develops or
increases, discontinue use and consult
a doctor.

Directions
Cleanse the skin thoroughly before
applying medication. • Cover the entire
affected area with a thin layer one to three
times daily. • Because excessive drying of
the skin may occur, start with one
application daily, then gradually increase
to two or three times daily if needed or as
directed by a doctor. • If bothersome
dryness or peeling occurs, reduce
application to once a day or every other day.

Inactive Ingredients
Water (Aqua), SD Alcohol 40-B, Hamamelis
Virginiana (Witch Hazel) Bark/Leaf/Twig
Extract, Butylene Glycol, Glycerin, Glycolic
Acid, Sodium Lactate, Linoleamidopropyl
PG-Dimonium Chloride Phosphate,
Hydroxyethylcellulose, Sodium Hydroxide,
Fragrance (Parfum), Polysorbate 20,
Polyquaternium-10, Hydrolyzed Algin,
Linalool, Propylene Glycol, Sea Salt (Maris
Sal), Palmaria Palmata Extract, Crithmum
Maritimum Extract, Himanthalia Elongata
Extract, Gigartina Stellata Extract,
Macrocystis Pyrifera Extract, Zinc Sulfate

Questions? call 1-800-242-2284
M-F, 8am-6pm CST

picture of carton label aacc272.jpg